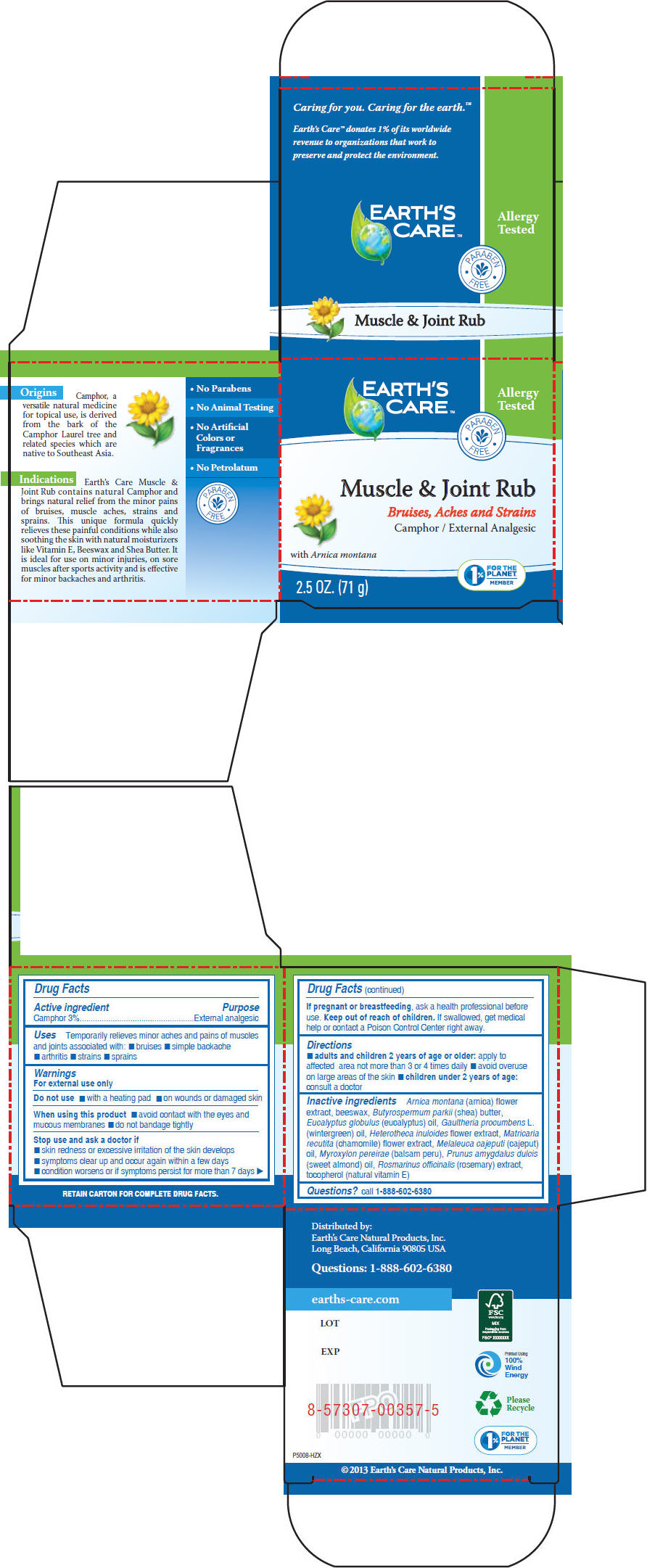 DRUG LABEL: EARTHS CARE MUSCLE AND JOINT RUB
NDC: 24286-1563 | Form: OINTMENT
Manufacturer: DLC Laboratories, Inc.
Category: otc | Type: HUMAN OTC DRUG LABEL
Date: 20260107

ACTIVE INGREDIENTS: CAMPHOR (NATURAL) 3 g/100 g
INACTIVE INGREDIENTS: ARNICA MONTANA FLOWER; BALSAM PERU; CAJUPUT OIL; CHAMOMILE; EUCALYPTUS OIL; ROSEMARY; SHEA BUTTER; ALMOND OIL; TOCOPHEROL; METHYL SALICYLATE; HETEROTHECA INULOIDES FLOWER

EARTH'S CARE™MUSCLE & JOINT RUB

Drug Facts

Active ingredient

Camphor 3%

Purpose

External analgesic

Uses

Temporarily relieves minor aches and pains of muscles and joints associated with:

- bruises
- simple backache
- arthritis
- strains
- sprains

Warnings

For external use only

Do not use

- with a heating pad
- on wounds or damaged skin

When using this product

- avoid contact with the eyes and mucous membranes
- do not bandage tightly

Stop use and ask a doctor if

- skin redness or excessive irritation of the skin develops
- symptoms clear up and occur again within a few days
- condition worsens or if symptoms persist for more than 7 days

PREGNANCY OR BREAST FEEDING

If pregnant or breastfeeding, ask a health professional before use.

Keep out of reach of children.If swallowed, get medical help or contact a Poison Control Center right away.

Directions

- adults and children 2 years of age or older:apply to affected area not more than 3 or 4 times daily
- avoid overuse on large areas of the skin
- children under 2 years of age:consult a doctor

Inactive ingredients

Arnica montana(arnica) flower extract, beeswax, Butyrospermum parkii(shea) butter, Eucalyptus globulus(eucalyptus) oil, Gaultheria procumbensL .(wintergreen) oil, Heterotheca inuloidesflower extract, Matricaria recutita(chamomile) flower extract, Melaleuca cajeputi(cajeput) oil, Myroxylon pereirae(balsam peru), Prunus amygdalus dulcis(sweet almond) oil, Rosmarinus officinalis(rosemary) extract, tocopherol (natural vitamin E)

Questions?

call 1-888-602-6380

Distributed by:
Earth's Care Natural Products, Inc.
Long Beach, California 90805 USA

PRINCIPAL DISPLAY PANEL - 71 g Jar Box

EARTH'S
CARE™

Allergy
Tested

PARABEN
FREE

Muscle & Joint Rub

Bruises, Aches and Strains

Camphor / External Analgesic

with Arnica montana

2.5 OZ. (71 g)

1%
FOR THE
PLANET℠
MEMBER